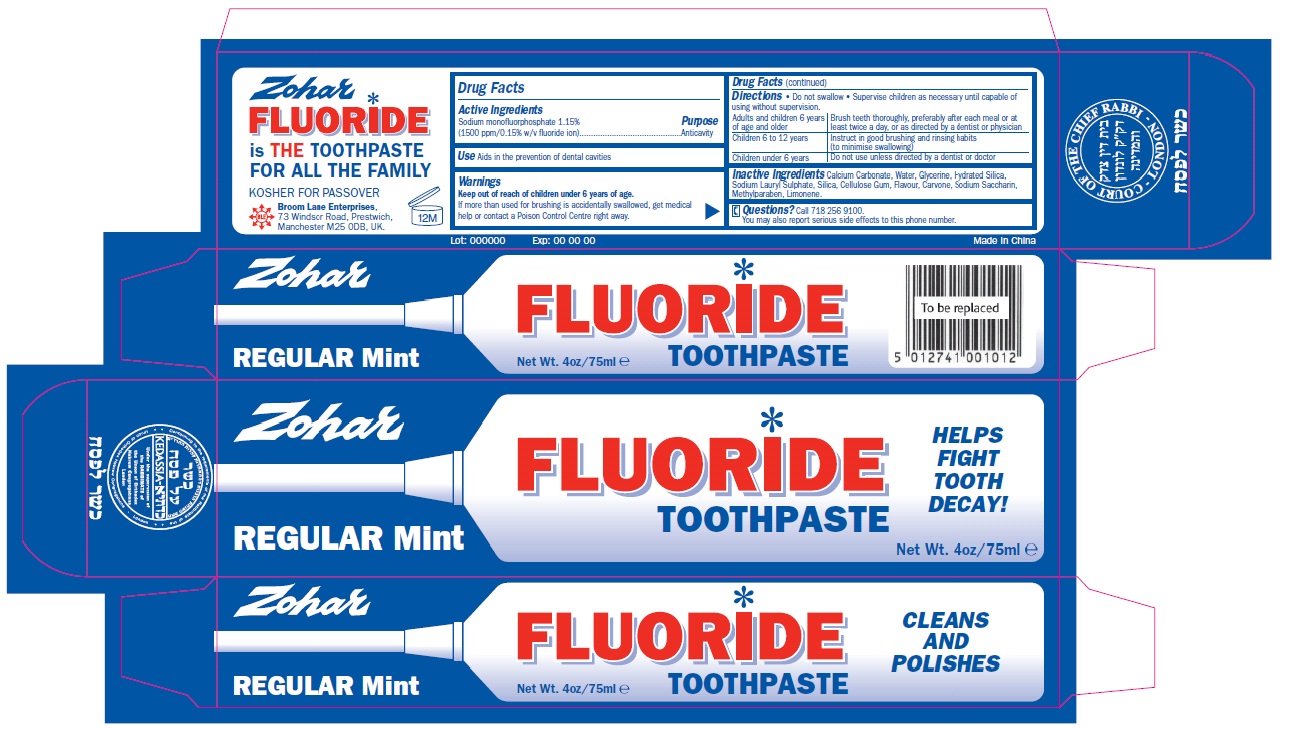 DRUG LABEL: Zohar Toothpaste
NDC: 55754-123 | Form: PASTE, DENTIFRICE
Manufacturer: Broom Lane Enterprises
Category: otc | Type: HUMAN OTC DRUG LABEL
Date: 20110228

ACTIVE INGREDIENTS: SODIUM MONOFLUOROPHOSPHATE 11.5 mg/1 g
INACTIVE INGREDIENTS: CALCIUM CARBONATE; WATER; GLYCERIN; HYDRATED SILICA; SODIUM LAURYL SULFATE; SILICON DIOXIDE; CARBOXYMETHYLCELLULOSE SODIUM; CARVONE, (+/-)-; SACCHARIN SODIUM; METHYLPARABEN

Drug Facts

Active Ingredients

Sodium monofluorphosphate 1.15% (1500 ppm/ 0.15% w/v fluoride ion)

Purpose

Anticavity

Uses

Aids in the prevention of dental cavities

Warnings

- keep out of reach of children under 6 years of age.
- If more than used for brushing is accidentally swallowed, get medical help or contact a poison control center right away.

Directions

- do not swallow
- supervise children as necessary until capable of using without supervision.

adults and children 6 years of age and older | Brush teeth thoroughly, preferably after each meal or at least twice a day, or as directed by a dentist or physician.
children 6 to 12 years | instruct in good brushing and rinsing habits(to minimise swallowing)
children under 6 years | do not use unless directed by dentist or doctor

INACTIVE INGREDIENT

Calcium Carbonate, Water, Glycerine, Hydrated Silica, Sodium Lauryl Sulphate, Silica, Cellulose gum, Flavour, Carvone, Sodium Saccharin, Methylparaben, Limonene

Questions?

call 718 256 9100
you may also report serious side effects to this phone number

Principal Display Panel

Zohar
FLUORIDE
TOOTHPASTE
REGULAR MINT

HELPS FIGHT TOOTH DECAY

Net Wt. 4oz/75ml